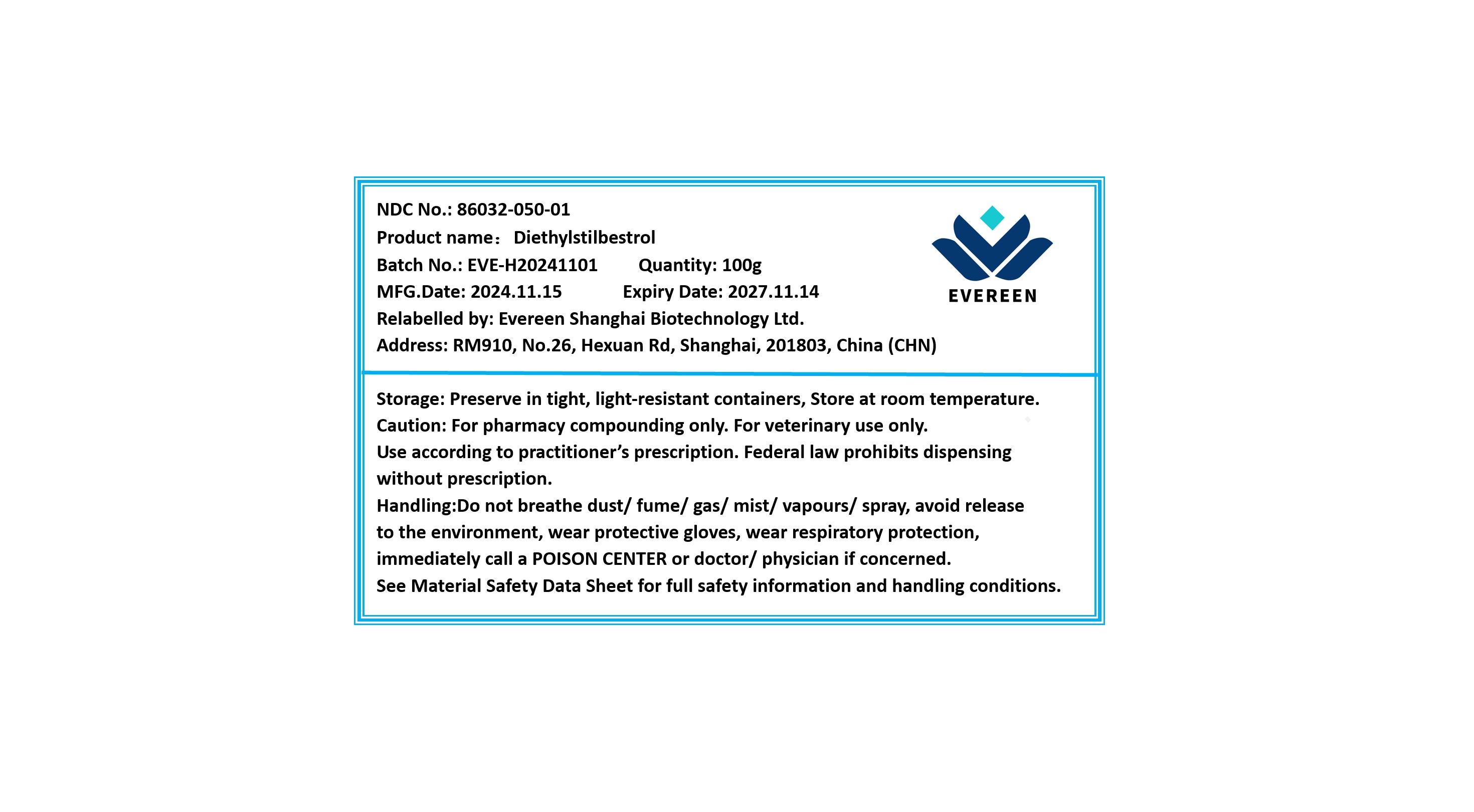 DRUG LABEL: Diethylstilbestrol
NDC: 86032-050 | Form: POWDER
Manufacturer: Evereen Shanghai Biotechnology Ltd.
Category: other | Type: BULK INGREDIENT - ANIMAL DRUG
Date: 20250604

ACTIVE INGREDIENTS: DIETHYLSTILBESTROL 1 g/1 g

Diethylstilbestrol